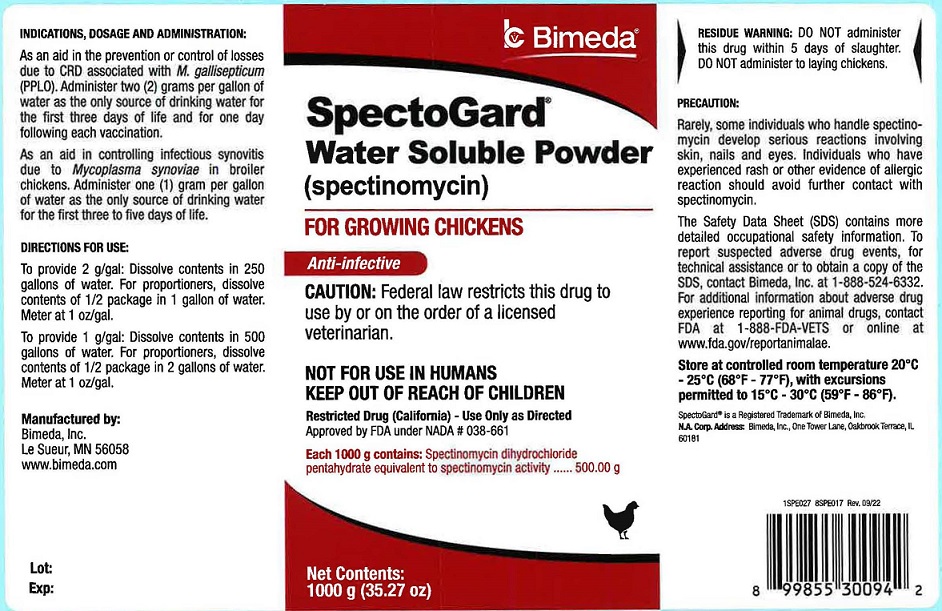 DRUG LABEL: SpectoGard Water Soluble Powder
NDC: 61133-5485 | Form: POWDER, FOR SOLUTION
Manufacturer: Bimeda, Inc.
Category: animal | Type: PRESCRIPTION ANIMAL DRUG LABEL
Date: 20231206

ACTIVE INGREDIENTS: SPECTINOMYCIN 500 g/1000 g

INDICATIONS AND USAGE

SpectoGard® Water Soluble Powder
(spectinomycin)
FOR GROWING CHICKENS
Anti-infective
CAUTION: Federal law restricts this drug to use by or on the order of a licensed veterinarian.
NOT FOR USE IN HUMANS
KEEP OUT OF REACH OF CHILDREN
Restricted Drug (California) - Use only as directed
Approved by FDA under NADA # 038-661

INDICATIONS, DOSAGE AND ADMINISTRATION:

As an aid in the prevention or control of losses due to CRD associated with M. gallisepticum (PPLO). Administer two (2) grams per gallon of water as the only source of drinking water for the first three days of life and for one day following each vaccination.

As an aid in controlling infectious synovitis due to Mycoplasma synoviae in broiler chickens. Administer one (1) gram per gallon of water as the only source of drinking water for the first three to five days of life.

DOSAGE AND ADMINISTRATION

DIRECTIONS FOR USE:
To provide 2 g/gal: Dissolve contents in 250 gallons of water. For proportioners, dissolve contents of 1/2 package in 1 gallon of water. Meter at 1 oz/gal.

To provide 1 g/gal: Dissolve contents in 500 gallons of water. For proportioners, dissolve contents of 1/2 package in 2 gallons of water. Meter at 1 oz/gal.

RESIDUE WARNING

RESIDUE WARNING: DO NOT administer this drug within 5 days of slaughter. DO NOT administer to laying chickens.

PRECAUTIONS

PRECAUTION:
Rarely, some individuals who handle spectinomycin develop serious reactions involving skin, nails and eyes. Individuals who have experienced rash or other evidence of allergic reaction should avoid further contact with spectinomycin.

The Safety Data Sheet (SDS) contains more detailed occupational safety information. To report suspected adverse drug events, for technical assistance or to obtain a copy of the SDS, contact Bimeda, Inc. at 1888-524-6332. For additional information about adverse drug experience reporting for animal drugs, contact FDA at 1-888-FDA-VETS or online at www.fda.gov/reportanimalae.

STORAGE AND HANDLING

Store at controlled room temperature 20°C - 25°C (68°F - 77°F), with excursions permitted 15°C - 30°C (59°F - 86°F).